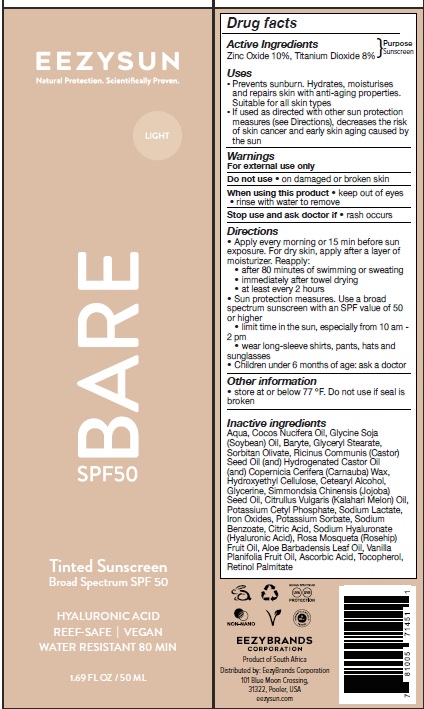 DRUG LABEL: Eezysun Bare SPF 50 Tinted Sunscreen Light
NDC: 70116-015 | Form: CREAM
Manufacturer: BIO EARTH MANUFACTURING (PTY) LTD
Category: otc | Type: HUMAN OTC DRUG LABEL
Date: 20240209

ACTIVE INGREDIENTS: TITANIUM DIOXIDE 8 g/100 mL; ZINC OXIDE 10 g/100 mL
INACTIVE INGREDIENTS: ALOE VERA LEAF; WATER; ASCORBIC ACID; BARIUM SULFATE; CETOSTEARYL ALCOHOL; CITRIC ACID MONOHYDRATE; CITRUS X LIMON FLOWERING TOP OIL; COCONUT OIL; CARNAUBA WAX; GLYCERIN; GLYCERYL MONOSTEARATE; SOYBEAN OIL; HYDROXYETHYL CELLULOSE, UNSPECIFIED; HYDROGENATED CASTOR OIL; FERRIC OXIDE RED; POTASSIUM CETYL PHOSPHATE; POTASSIUM SORBATE; VITAMIN A PALMITATE; CASTOR OIL; ROSA MOSCHATA OIL; JOJOBA OIL; SODIUM BENZOATE; HYALURONATE SODIUM; SODIUM LACTATE; SORBITAN OLIVATE; .ALPHA.-TOCOPHEROL ACETATE; VANILLA PLANIFOLIA OIL

Active ingredients

Zinc Oxide 10%, Titanium Dioxide 8%

Purpose

Sunscreen

Uses

- Prevents sunburn, Hydrates, Moisturizes and repairs skin with anti-aging properties. Suitable for all skin types.
- If used as directed with other sun protection measures (see Directions), decreases the risk of skin cancer and early skin aging caused by the sun

Warnings

For external use only
Do not use on damaged or broken skin
When using this product keep out of eyes.
rinse with water to remove
Stop use and ask doctor if rash occurs
Keep out of reach of children

Direction

- Apply every morning or 15 min before sun exposure. For dry skin, apply after a layer of moisturizer. Reapply:
- after 80 minutes of swimming or sweating
- immediately after towel drying
- at least every 2 hours
- Sun protection measures. Use a broad spectrum sunscreen with an SPF value of 50 or higher
- limit time in the sun, especially from 10 am -2 pm
- wear long-sleeve shirts, pants, hats and sunglasses
- Children under 6 months of age: ask a doctor

Other information

Store at or below 77℉. Do not use if seal is broken

Inactive ingredients

Aqua, Cocos Nucifera Oil, Glycine Soja (Soybean) Oil, Baryte, Glyceryl Stearate, Sorbitan Olivate, Ricinus Communis (Castor) Seed Oil (and) Hydrogenated Castor Oil (and) Copernicia Cerifera (Carnauba) Wax,Hydroxyethyl Cellulose, Cetearyl Alcohol, Glycerine, Simmondsia Chinensis (Jojoba)Seed Oil, Citrullus Vulgaris (Kalahari Melon) Oil, Potassium Cetyl Phosphate, Sodium Lactate, Iron Oxides, Potassium Sorbate, Sodium
Benzoate, Citric Acid, Sodium Hyaluronate (Hyaluronic Acid), Rosa Mosqueta (Rosehip) Fruit Oil, Aloe Barbadensis Leaf Oil, Vanilla Planifolia Fruit Oil, Ascorbic Acid, Tocopherol, Retinol Palmitate